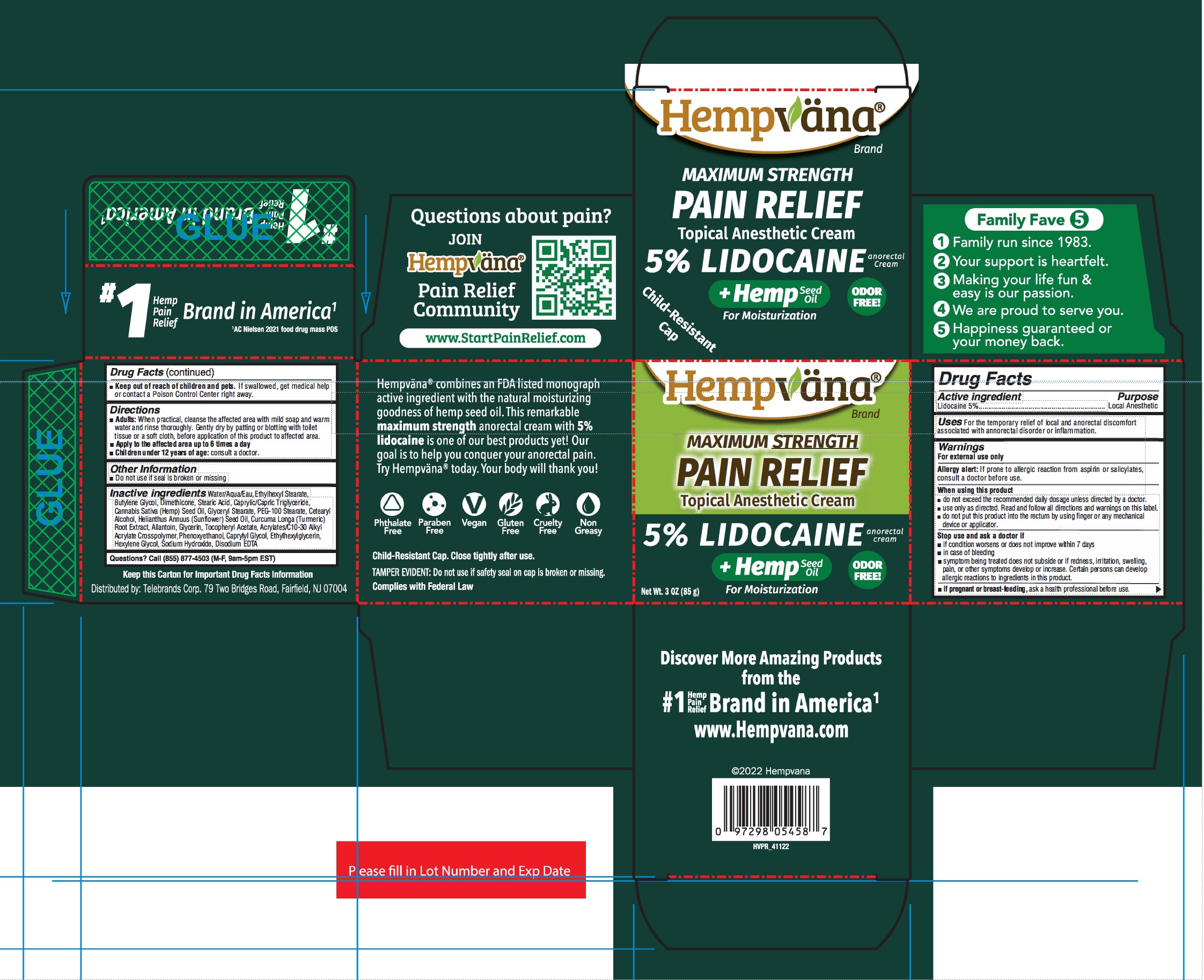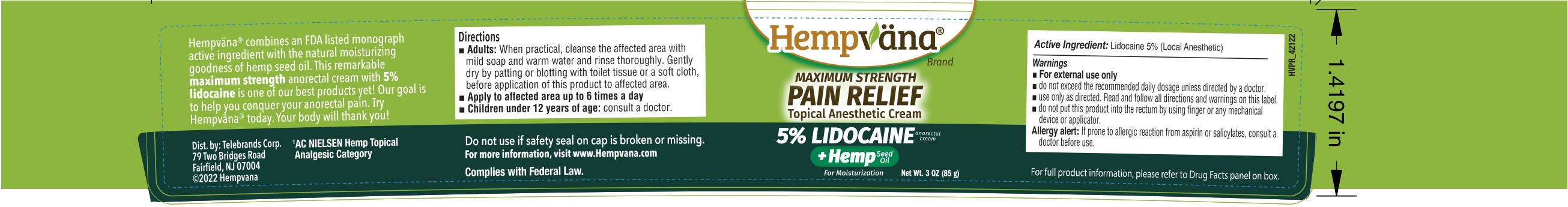 DRUG LABEL: Hempvana Maximum Strength Pain Relief Topical Anesthetic
NDC: 73287-026 | Form: CREAM
Manufacturer: Telebrands Corp
Category: otc | Type: HUMAN OTC DRUG LABEL
Date: 20241120

ACTIVE INGREDIENTS: LIDOCAINE 5 g/100 g
INACTIVE INGREDIENTS: CANNABIS SATIVA SEED OIL; .ALPHA.-TOCOPHEROL ACETATE; TURMERIC; GLYCERYL MONOSTEARATE; PEG-100 STEARATE; CAPRYLYL GLYCOL; PHENOXYETHANOL; ETHYLHEXYLGLYCERIN; MEDIUM-CHAIN TRIGLYCERIDES; GLYCERIN; CETOSTEARYL ALCOHOL; ALLANTOIN; BUTYLENE GLYCOL; SODIUM HYDROXIDE; EDETATE DISODIUM ANHYDROUS; SUNFLOWER SEED; WATER; STEARIC ACID; CARBOMER INTERPOLYMER TYPE A (ALLYL SUCROSE CROSSLINKED); ETHYLHEXYL STEARATE; HEXYLENE GLYCOL

Hempvana Topical Anesthetic Cream

Active ingredient

Lidocaine 5%

Purpose

Lidocaine 5%...........Local Anesthetic

Uses

For the temporary relief of local and anorectal discomfort associated with anorectal disorder or inflammation.

Warnings

For external use only

Allergy alert:If prone to allergic reaction from aspirin or salicylates, consult a doctor before use.

When using this product

- do not exceed the recommended daily dosage unless directed by a doctor.
- use only as directed. Read and follow all directions and warnings on this label.
- do not put this product into the rectum by using finger or any mechanical device or applicator.

Stop use and ask a doctor if

- condition worsens or does not improve within 7 days
- in case of bleeding
- symptom being treated does not subside or if redness, irritation, sweeling, pain, or other symptoms develop or increase. Certain persons can develop allergic reactions to ingredients in this product.

PREGNANCY OR BREAST FEEDING

If pregnant or breast-feeding, ask a health professional before use.

Keep out of reach of children and pets.If swallowed, get medical help or contact a Poison Control Center right away.

Directions

- Adults:When practical, cleanse the affected area with mild soap and warm water and rinse thoroughly. Gently dry by patting or blotting with toilet tissue or a soft cloth, before application of this product to affected area.
- Apply to the affected area up to 6 times a day
- Children under 12 years of age:consult a doctor.

Other information

- Do not use if seal is broken or missing

Inactive ingredients

Water/Aqua/Eau, Ethylhexyl Stearate, Butylene Glycol, Dimethicone, Stearic Acid, Caprylic/Capric Triglyceride, Cannabis Saliva (Hemp) Seed Oil, Glyceryl Stearate, PEG-100 Stearate, Cetearyl Alcohol, Helianthus Annuus (Sunflower) Seed Oil, Curcuma Longa (Turmeric) Root Extract, Allantoin, Glycerin, Tocopheryl Acetate, Acrylates/C10-30 Alkyl Acrylate Crosspolymer, Phenoxyethanol, Caprylyl Glycol, Ethylhexylglycerin, Hexylene Glycol, Sodium Hydroxide, Disodium EDTA

Questions?

Call (855) 877-4503 (M-F, 9am-5pm EST)

PACKAGE LABEL

Hempvana

Maximum Strength Pain Relief Topical Anesthetic Cream

5% Lidocaine anorectal cream

+Hemp Seed Oil For Moisturization

Odor Free!

Net Wt. 3 oz (85 g)